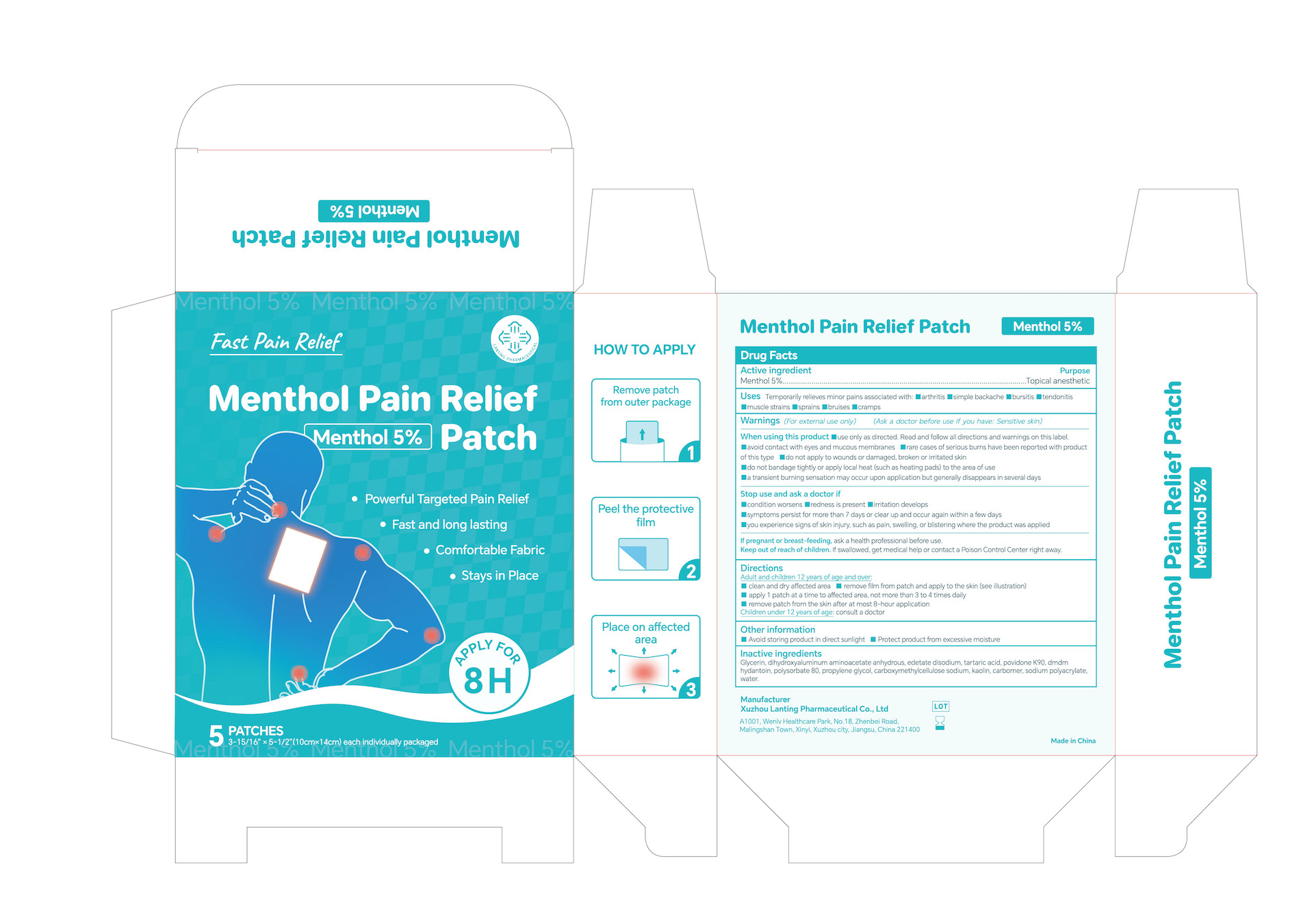 DRUG LABEL: 5% Menthol Pain Relief Patch
NDC: 85323-004 | Form: PATCH
Manufacturer: Xuzhou Lanting Pharmaceutical Co., Ltd
Category: otc | Type: HUMAN OTC DRUG LABEL
Date: 20250301

ACTIVE INGREDIENTS: LEVOMENTHOL 5 g/100 g
INACTIVE INGREDIENTS: WATER; POLYSORBATE 80; KAOLIN; SODIUM POLYACRYLATE (2500000 MW); CARBOMER; GLYCERIN; DMDM HYDANTOIN; PROPYLENE GLYCOL; CARBOXYMETHYLCELLULOSE SODIUM; EDETATE DISODIUM; DIHYDROXYALUMINUM AMINOACETATE ANHYDROUS; POVIDONE K90; TARTARIC ACID

5% Menthol Pain Relief Patch, Package NDC Code 85323-004-00

Active Ingredient

Active Ingredient: 5% Menthol

Purpose

Topical anesthetic

Warnings

Warnings (For external use only)

- Do not use
- more than 1 patch at a time
- on wounds or damaged skin
- with a heating pad
- if you are allergic to any ingredients of this product

When using this product

- use only as directed
- avoid contact with the eyes, mucous membranes or rashes
- do not bandage tightly

Stop use and ask a doctor if

- condition worsens
- redness is present
- irritation develops
- symptoms persist for more than 7 days or clear up and occur again within a few days
- you experience signs of skin injury, such as pain, swelling, or blistering where the product was applied

If pregnant or breast-feeding, ask a health professional before use.

Keep out of reach of children. If swallowed, get medical help or contact a Poison Control Center right away.

Inactive Ingredients

Glycerin, dihydroxyaluminum aminoacetate anhydrous, edetate disodium, tartaric acid, povidone K90, dmdm hydantoin, polysorbate 80, propylene glycol, carboxymethylcellulose sodium, kaolin, carbomer, sodium polyacrylate, water.

Keep out of reach of children. If swallowed, get medical help or contact a Poison Control Center right away.

Other information

- Avoid storing product in direct sunlight
- Protect product from excessive moisture

DOSAGE AND ADMINISTRATION

Adult and children 12 years of age and over:
clean and dry affected area
remove film from patch and apply to the skin (see illustration)
apply 1 patch at a time to affected area, not more than 3 to 4 times daily
remove patch from the skin after at most 8-hour application

Children under 12 years of age: consult a doctor

Uses

Temporarily relieves minor pains associated with:

arthritis

simple backache

bursitis

tendonitis

muscle strains

sprains

bruises

cramps

Directions

Uses For temporary relieves minor pains associated with:

arthritis
simple backache
bursitis
tendonitis
muscle strains
sprains
bruises
cramps

Adult and children 12 years of age and over:

clean and dry affected area

remove film from patch and apply to the skin (see illustration)

apply 1 patch at a time to affected area, not more than 3 to 4 times daily

remove patch from the skin after at most 8-hour application

Children under 12 years of age: consult a doctor